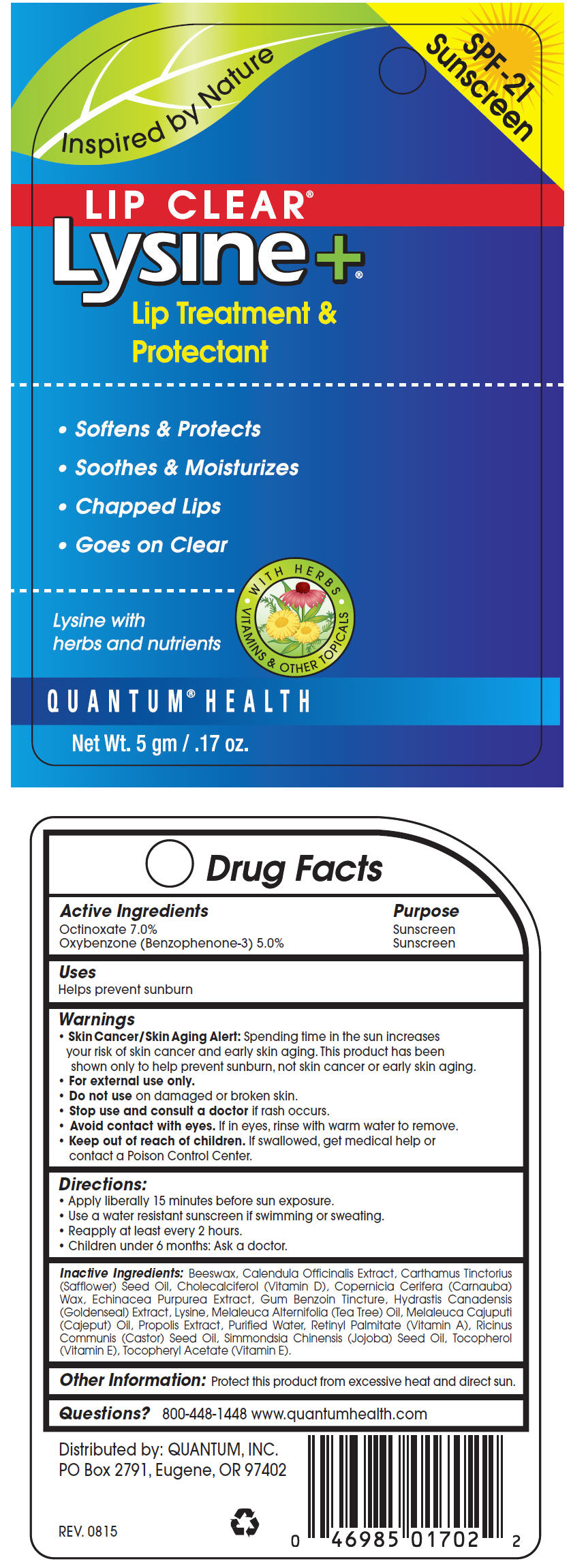 DRUG LABEL: Lip Clear Lysine Plus Coldstick
NDC: 70084-210 | Form: LIPSTICK
Manufacturer: Quantum, Inc.
Category: otc | Type: HUMAN OTC DRUG LABEL
Date: 20251020

ACTIVE INGREDIENTS: OCTINOXATE 70 mg/1 g; OXYBENZONE 50 mg/1 g
INACTIVE INGREDIENTS: YELLOW WAX; CALENDULA OFFICINALIS FLOWER; ECHINACEA PURPUREA; BENZOIN RESIN; GOLDENSEAL; LYSINE HYDROCHLORIDE; TEA TREE OIL; MELALEUCA CAJUPUTI LEAF OIL; PROPOLIS WAX; VITAMIN A PALMITATE; SAFFLOWER; CHOLECALCIFEROL; CARNAUBA WAX; WATER; CASTOR OIL; JOJOBA OIL; .ALPHA.-TOCOPHEROL ACETATE; TOCOPHEROL

Lip Clear®Lysine +®Coldstick

Drug Facts

ACTIVE INGREDIENT

Active Ingredients | Purpose
Octinoxate 7.0% | Sunscreen
Oxybenzone (Benzophenone-3) 5.0% | Sunscreen

Uses

Helps prevent sunburn

Warnings

- Skin Cancer/Skin Aging Alert:Spending time in the sun increases your risk of skin cancer and early skin aging. This product has been shown only to help prevent sunburn, not skin cancer or early skin aging.
- For external use only.

- Do not useon damaged or broken skin.

- Stop use and consult a doctorif rash occurs.
- Avoid contact with eyes.If in eyes, rinse with warm water to remove.

- Keep out of reach of children.If swallowed, get medical help or contact a Poison Control Center.

Directions

- Apply liberally 15 minutes before sun exposure.
- Use a water resistant sunscreen if swimming or sweating.
- Reapply at least every 2 hours.
- Children under 6 months: Ask a doctor.

Inactive Ingredients

Beeswax, Calendula Officinalis Extract, Carthamus Tinctorius (Safflower) Seed Oil, Cholecalciferol (Vitamin D), Copernicia Cerifera (Carnauba) Wax, Echinacea Purpurea Extract, Gum Benzoin Tincture, Hydrastis Canadensis (Goldenseal) Extract, Lysine, Melaleuca Alternifolia (Tea Tree) Oil, Melaleuca Cajuputi (Cajeput) Oil, Propolis Extract, Purified Water, Retinyl Palmitate (Vitamin A), Ricinus Communis (Castor) Seed Oil, Simmondsia Chinensis (Jojoba) Seed Oil, Tocopherol (Vitamin E), Tocopheryl Acetate (Vitamin E).

Other Information

Protect this product from excessive heat and direct sun.

Questions?

800-448-1448 www.quantumhealth.com

Distributed by: QUANTUM, INC.
PO Box 2791, Eugene, OR 97402

PRINCIPAL DISPLAY PANEL - 5 gm Cylinder Blister Pack

Inspired by Nature

SPF-21
Sunscreen

LIP CLEAR®
Lysine+®

Lip Treatment &
Protectant

- Softens & Protects
- Soothes & Moisturizes
- Chapped Lips
- Goes on Clear

Lysine with
herbs and nutrients

• WITH HERBS • VITAMINS & OTHER TOPICALS

QUANTUM®HEALTH

Net Wt. 5 gm / .17 oz.